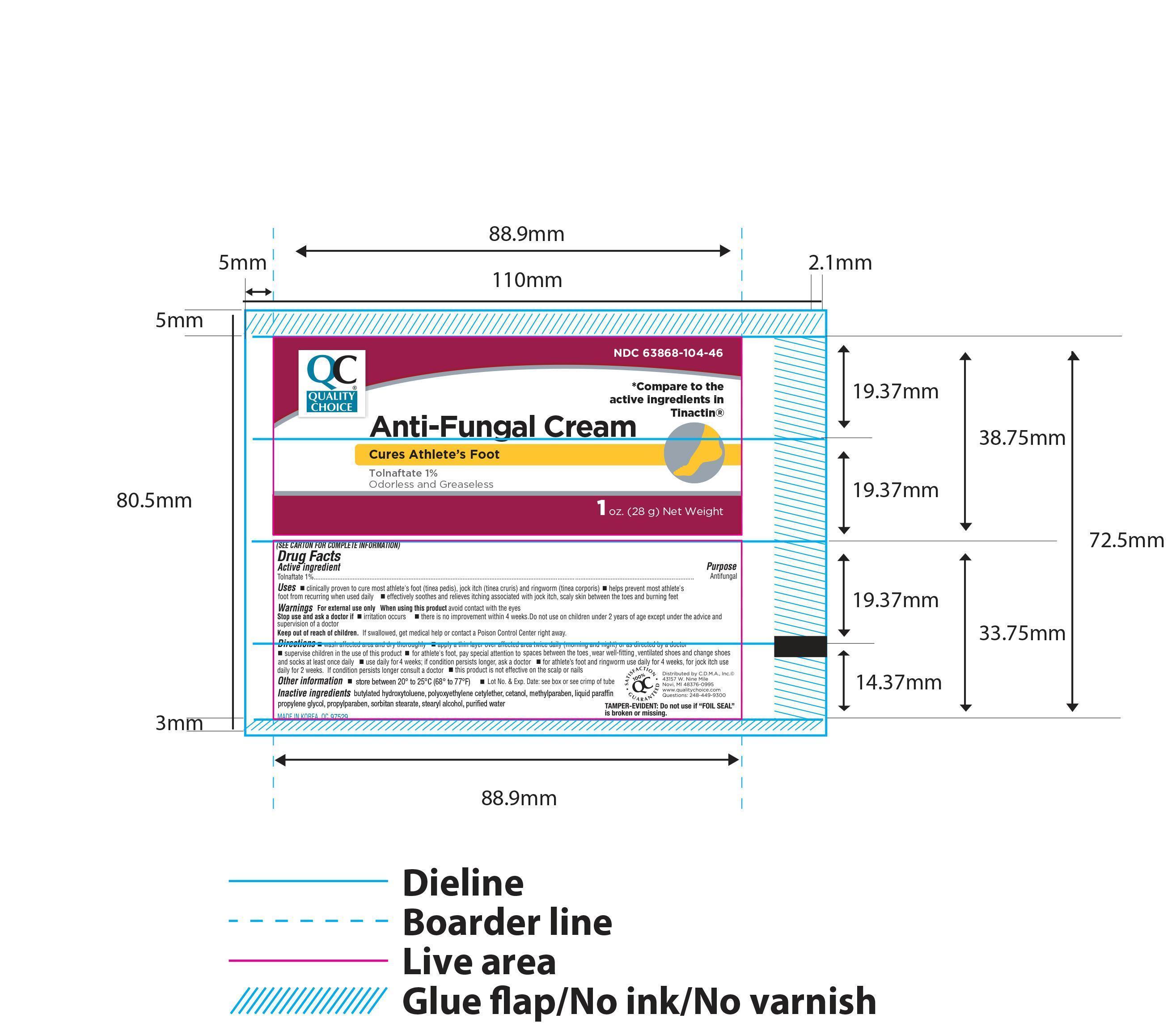 DRUG LABEL: Quality Choice Tolnaftate Antifungal
NDC: 63868-104 | Form: CREAM
Manufacturer: Chain Drug Marketing Association Inc
Category: otc | Type: HUMAN OTC DRUG LABEL
Date: 20171212

ACTIVE INGREDIENTS: TOLNAFTATE 1 g/100 g
INACTIVE INGREDIENTS: PROPYLENE GLYCOL; MINERAL OIL; STEARYL ALCOHOL; CETYL ALCOHOL; SORBITAN MONOSTEARATE; WATER; METHYLPARABEN; PROPYLPARABEN

QC Anti-Fungal Cream 1oz NBE Tinactin

Active ingredient Purpose

Tolnaftate 1%....................................................................Antifungal

Uses

- clinically proven to cure most athlete's foot (tinea pedis), jock itch (tinea cruris) and ringworm (tinea corporis)
- helps prevent most athlete's foot recurring when used daily
- effectively soothes and relieves itching associated with jock itch, scaly skin between the toes and burning feet

Warnings For external use only

When using this product avoid contact with the eyes

Stop use and ask a doctor if

- irritation occurs
- there is no improvement within 4 weeks

Do not use on children under 2 years of age except under the advice and supervision of a doctor.

Keep out of reach of children. If swallowed, get medical help or contact a Poison Control Center right away.

Directions

- wash affected area and dry thoroughly
- apply a thin layer over affected area twice daily (morning and night) or as directed by a doctor
- supervise children in the use of this product for athlete's foot, pay special attention to space between the toes, wear well-fitting, ventilated shoes and change shoes and socks at least one daily
- use daily for 4 weeks; if condition persists longer, ask a doctor
- for athlete's foot and ringworm use daily for 4 weeks, for jock itch use daily for 2 weeks. If condition persists longer consult a doctor
- this product is not effective on the scalp or nails

Other information

- store between 2° and 30° C (36° and 86° F)
- Lot No. and Exp. Date:see box or see crimp of tube

INACTIVE INGREDIENT

Inactive ingredients propylene glycol, liquid paraffin, stearyl alcohol, cetyl alcohol, sorbitan monostearate, polyoxyethylene cetylether, purified water, methylparaben, propylparaben

DOSAGE AND ADMINISTRATION

Distributed By Quality Choice

Novi, Mi 48376-0995

Made in Korea